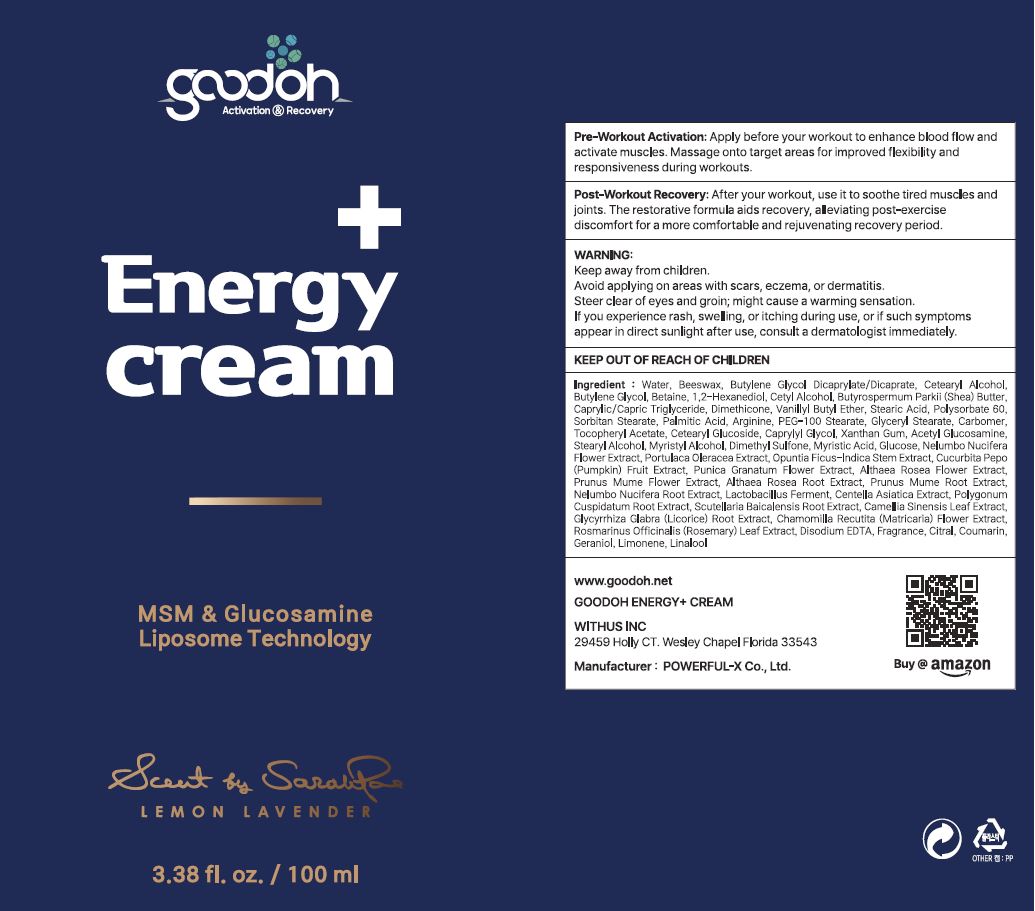 DRUG LABEL: Goodoh EnergyCream
NDC: 70042-0016 | Form: CREAM
Manufacturer: PowerfulX
Category: otc | Type: HUMAN OTC DRUG LABEL
Date: 20231130

ACTIVE INGREDIENTS: DIMETHYL SULFONE 1 g/100 mL; N-ACETYLGLUCOSAMINE 1 g/100 mL
INACTIVE INGREDIENTS: WATER

Drug Facts

ACTIVE INGREDIENT

Glucosamine, Dimethyl Sulfone

INACTIVE INGREDIENT

Water, etc

PURPOSE

Massage and Recovery cream

keep out of reach of the children

WARNINGS

Consult a physician if you have any abnormal symptoms such as red spots, swelling or itching, or side effects caused by direct sunlight.

DOSAGE AND ADMINISTRATION

for external use only

INDICATIONS AND USAGE

Apply a proper amount of this product to skin 10 minutes before exercise.

After shower, apply to skin and massage.